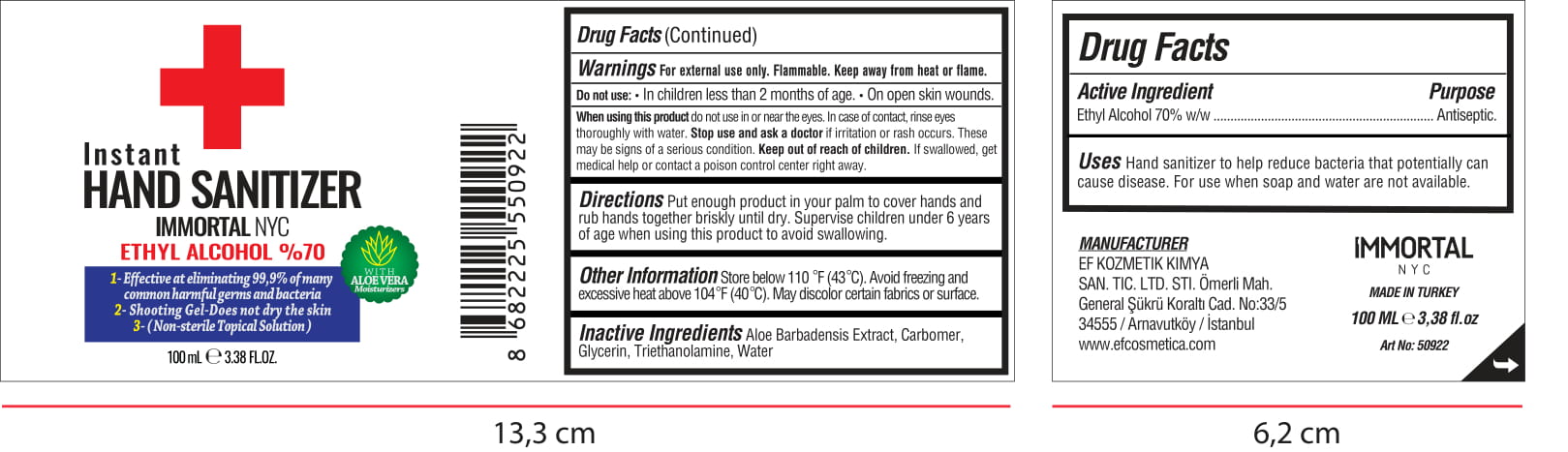 DRUG LABEL: IMMORTAL NYC HAND SANITIZER
NDC: 86822-001 | Form: GEL
Manufacturer: EF KOZMETIK KIMYA SANAYI VE TICARET LIMITED SIRKETI
Category: otc | Type: HUMAN OTC DRUG LABEL
Date: 20200620

ACTIVE INGREDIENTS: ALCOHOL 70 mL/100 mL
INACTIVE INGREDIENTS: GLYCERIN 1 mL/100 mL; TROLAMINE 0.3 mL/100 mL; WATER 28.39 mL/100 mL; CARBOMER 940 0.3 mL/100 mL; ALOE VERA LEAF 0.01 mL/100 mL

IMMORTAL NYC HAND SANITIZER

This is a hand sanitizer manufactured according to the Temporary Policy for Preparation of Certain Alcohol-Based Hand Sanitizer Products During the Public Health Emergency (CoViD-19); Guidance for Industry.

The hand sanitizer is manufactured using only the following United States Pharmacopoeia (USP) grade ingredients in the preparation of the product (percentage in final product formulation) consistent with World Health Organization (WHO) recommendations:

1. Alcohol (ethanol) (USP or Food Chemical Codex (FCC) grade) (70%, volume/volume (v/v)) in an aqueous solution denatured according to Alcohol and Tobacco Tax and Trade Bureau regulations in 27 CFR part 20.
2. Glycerol (1% v/v).
3. Triethanolamine (0.3% v/v).
4. Aloe Barbadensis Leaf Extract (0.01% v/v).
5. Carbomer (0.3% v/v).
6. Sterile distilled water or boiled cold water.

The firm does not add other active or inactive ingredients. Different or additional ingredients may impact the quality and potency of the product.

Active Ingredient(s)

Alcohol 70% v/v. Purpose: Antiseptic

Purpose

Antiseptic, Hand Sanitizer

Use

Hand Sanitizer to help reduce bacteria that potentially can cause disease. For use when soap and water are not available.

Warnings

For external use only. Flammable. Keep away from heat or flame

Do not use

- in children less than 2 months of age
- on open skin wounds

When using this product keep out of eyes. In case of contact with eyes, rinse eyes thoroughly with water.
Stop use and ask a doctor if irritation or rash occurs. These may be signs of a serious condition.
Keep out of reach of children. If swallowed, get medical help or contact a Poison Control Center right away.

Stop use and ask a doctor if irritation or rash occurs. These may be signs of a serious condition.

Keep out of reach of children. If swallowed, get medical help or contact a Poison Control Center right away.

Directions

- Put enough product in your palm to cover hands and rub hands together briskly until dry.
- Supervise children under 6 years of age when using this product to avoid swallowing.

Other information

- Store below 110 F (43 C).
- Avoid freezing and excessive heat above 40C (104F)
- May discolor certain fabrics or surface.

Inactive ingredients

Aloe Barbadensis Extract, Carbomer, Glycerin, Triethanolamine, Water

Package Label - Principal Display Panel

100 mL NDC: 86822-001-01